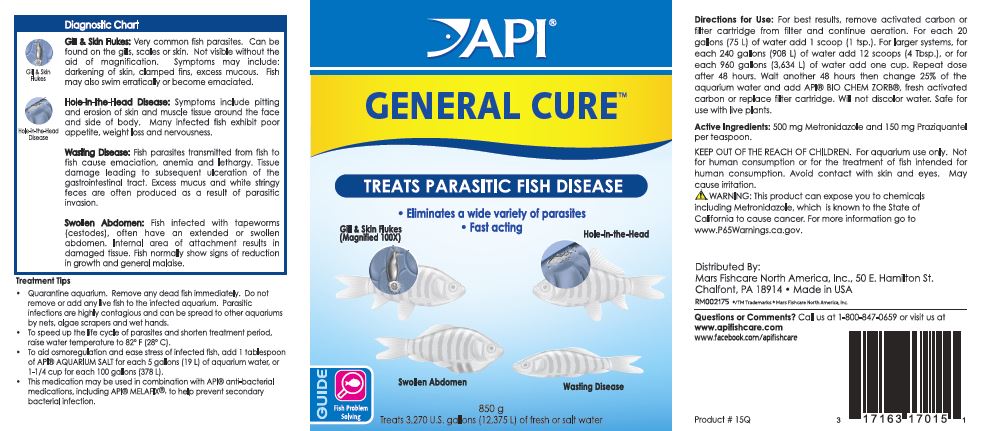 DRUG LABEL: API GENERAL CURE
NDC: 17163-016 | Form: POWDER
Manufacturer: MARS FISHCARE NORTH AMERICA, INC.
Category: animal | Type: OTC ANIMAL DRUG LABEL
Date: 20211229

ACTIVE INGREDIENTS: METRONIDAZOLE  500 mg/5.2 g; PRAZIQUANTEL 150 mg/5.2 g

Drug Label

ACTIVE INGREDIENT

Active Ingredients: 500 mg Metronidazole and 150 mg Praziquantel per teaspoon.

DOSAGE AND ADMINISTRATION

Directions for Use:

For best results, remove activated carbon or filter cartridge from filter and continue aeration.

For each 20 gallons (75 L) of water add 1 scoop (1 tsp.).

For larger systems, for each 240 gallons (908 L) of water add 12 scoops (4 Tbsp.). or for each 960 gallons (3,634 L) of water add one cup.

Repeat dose after 48 hours.

Wait another 48 hours then change 25% of the aquarium water and add API BIO CHEM ZORB, fresh activated carbon or replace filter cartridge.

Will not discolor water.

Safe for use with live plants

WARNINGS AND PRECAUTIONS

KEEP OUT OF THE REACH OF CHILDREN.

For aquarium use only.

Not for human consumption or for the treatment of fish intended for human consumption.

Avoid contact with skin and eyes.

May cause irritation.

! WARNING:

This product can expose you to chemicals including Metronidazole, which is known to the State of California to cause cancer.

For more information go to www.P65Warnings.ca.gov.

INDICATIONS AND USAGE

Diagnostic Chart

Gill and Skin Flukes:

Very common fish parasites. Can be found on the gills, scales or skin. Not visible without the aid of magnification. Symptoms may include: darkening of skin, clamped fins, excess mucous. Fish may also swim erratically or become emaciated.

Hole-in-the-Head Disease:

Symptoms include pitting and erosion of skin and muscle tissue around the face and side of body. Many infected fish exhibit poor appetite, weight loss and nervousness.

Wasting Disease:

Fish parasites transmitted fromn fish to fish cause emaciation, anemia and lethargy.Tissue damage leading to subsequent ulceration of the gastrointestinal tract. Excess mucus and white stringy feces are often produced as a result of parasitic invasion.

Swollen Abdomen:

Fish infected with tapeworms (cestodes), often have an extended or swollen abdomen. Internal area of attachment results in damaged tissue. Fish normally show signs of reduction ingrowth and general malaise.

Treatment Tips

Quarantine aquarium. Remove any dead fish immediately. Do not remove or add any live fish to the infected aquarium. Parasitic infections are highly contagious and can spread to other aquariums by nets, algae scrapers and wet hands.

To speed up the life cycle of parasites and shorten treatment period, raise water temperature to 82 F (28 C).

To aid osmoreregulation and ease stress of infected fish, add 1 tablespoon of API AQUARIUM SALT for each 5 gallons (19 L) of aquarium water, or 1 -1/4 cup for each 100 gallons (378 L).

This medication may be used in combination with API antibacterial medications, including API MELAFIX, to help prevent scondary bacterial infection.

PACKAGE LABEL

API

GENERAL CURE

TREATS PARASITIC FISH DISEASE

Eliminates a wide variety of parasites

Fastacting

Gill and Skin Flukes

Hole-in-the-Head

Swollen Abdomen

Wasting Disease

GUIDE

Fish Problem

Solving

850 g

Treats 3,270 U.S. gallons (12,375 L) of fresh or salt water